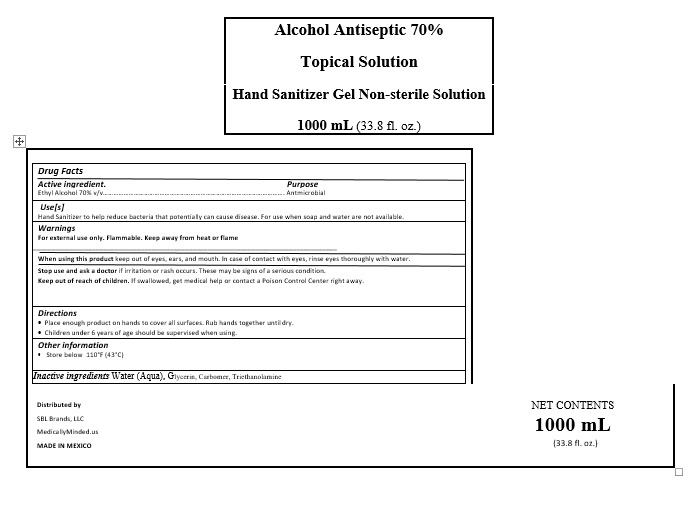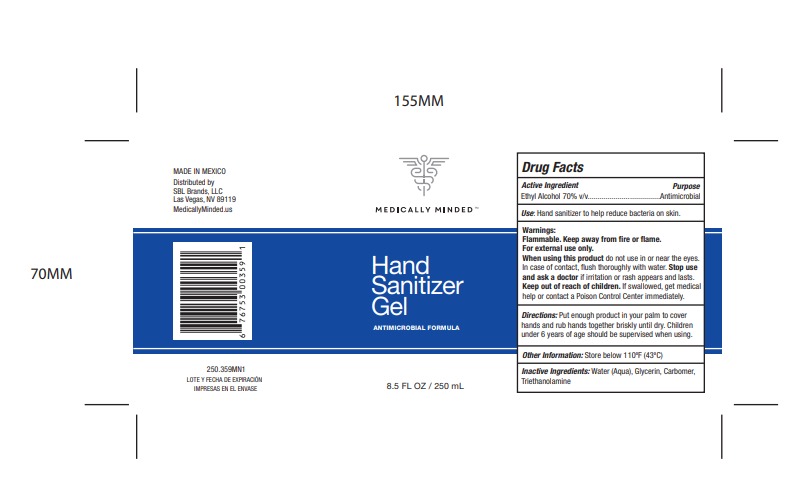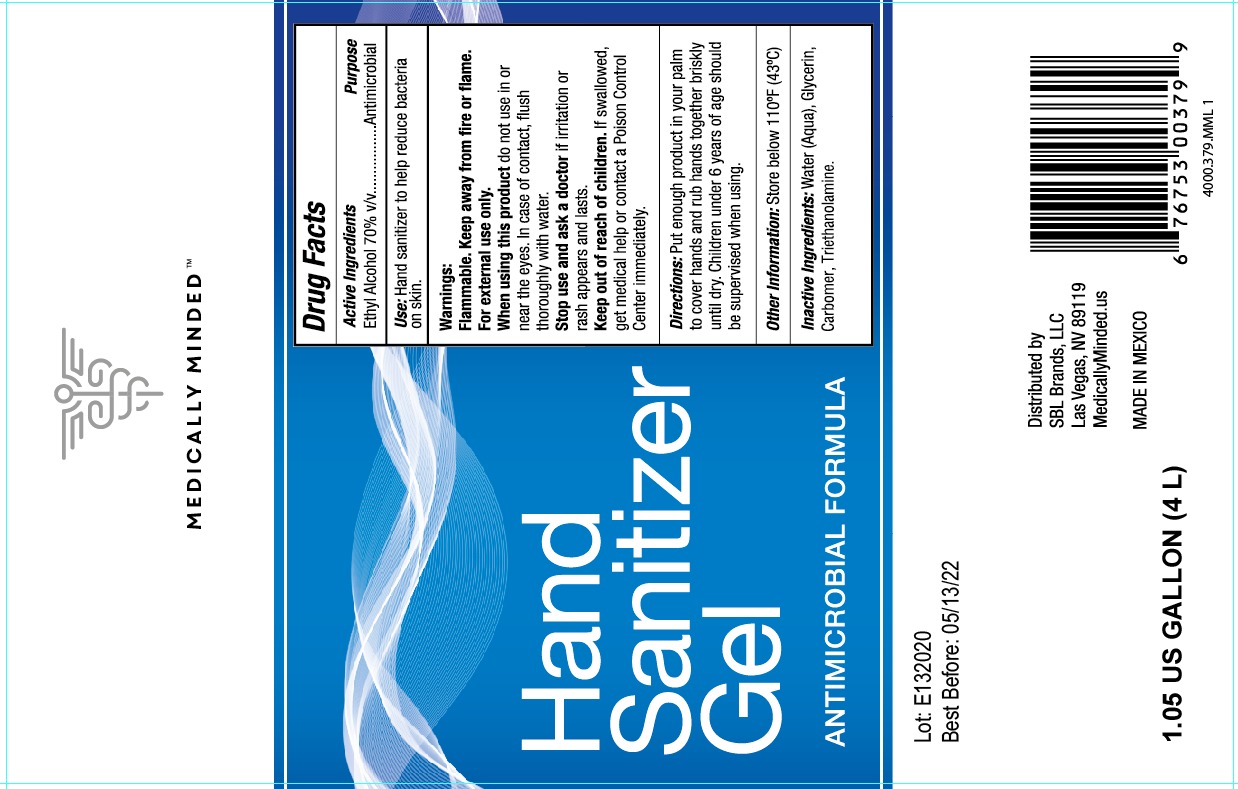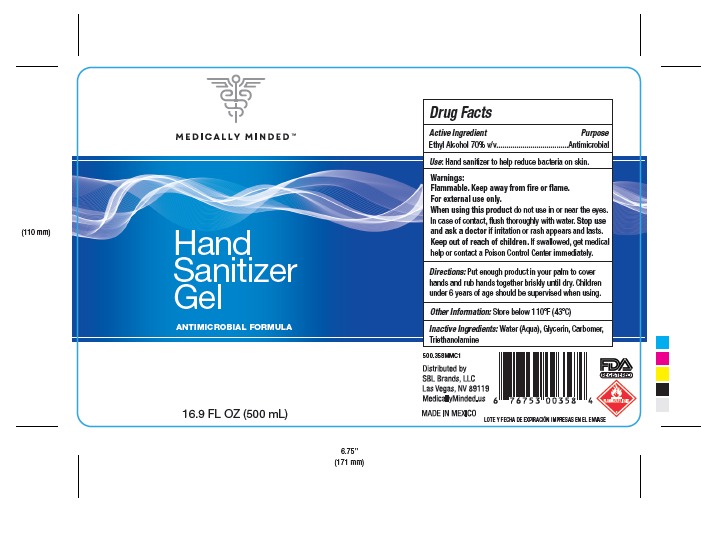 DRUG LABEL: HAND SANITIZER
NDC: 78501-1000 | Form: GEL
Manufacturer: COMERCIAL GOURA,S. DE R.L.
Category: otc | Type: HUMAN OTC DRUG LABEL
Date: 20200713

ACTIVE INGREDIENTS: ALCOHOL 0.7 mL/1 mL
INACTIVE INGREDIENTS: CARBOMER 940 0.002 mL/1 mL; GLYCERIN 0.0375 mL/1 mL; WATER 0.2585 mL/1 mL; TRIETHANOLAMINE CAPROYL GLUTAMATE 0.002 mL/1 mL

HAND SANITIZER

DIRECTION

Place enough product on hands to cover all surfaces. Rub hands together until dry.

INACTIVE INGREDIENT SECTION

Inactive ingredients Water (Aqua), Glycerin, Carbomer, Triethanolamine

INDICATIONS AND USAGE

Directions

Place enough product on hands to cover all surfaces. Rub hands together until dry.

Supervise children under 6 years of age when using this product to avoid swallowing.

When using this product keep out of eyes, ears, and mouth. In case of contact with eyes, rinse eyes thoroughly with water.

Keep out of reach of children. If swallowed, get medical help or contact a Poison Control Center right away.

PURPOSE SECTION

Purpose

Antmicrobial

WARNINGS AND PRECAUTIONS

Warnings

For external use only. Flammable. Keep away from heat or flame

When using this product keep out of eyes, ears, and mouth. In case of contact with eyes, rinse eyes thoroughly with water.

Store below 110°F (43°C)

ACTIVE INGREDIENT

Active ingredient. Ethyl Alcohol 70% v/v

ASK A DOCTOR

Stop use and ask a doctor if irritation or rash occurs. These may be signs of a serious condition.

ASK A DOCTOR

Stop use and ask a doctor if irritation or rash occurs. These may be signs of a serious condition.

STOP USE

Stop use and ask a doctor if irritation or rash occurs. These may be signs of a serious condition.

WARNING

Warnings

For external use only. Flammable. Keep away from heat or flame